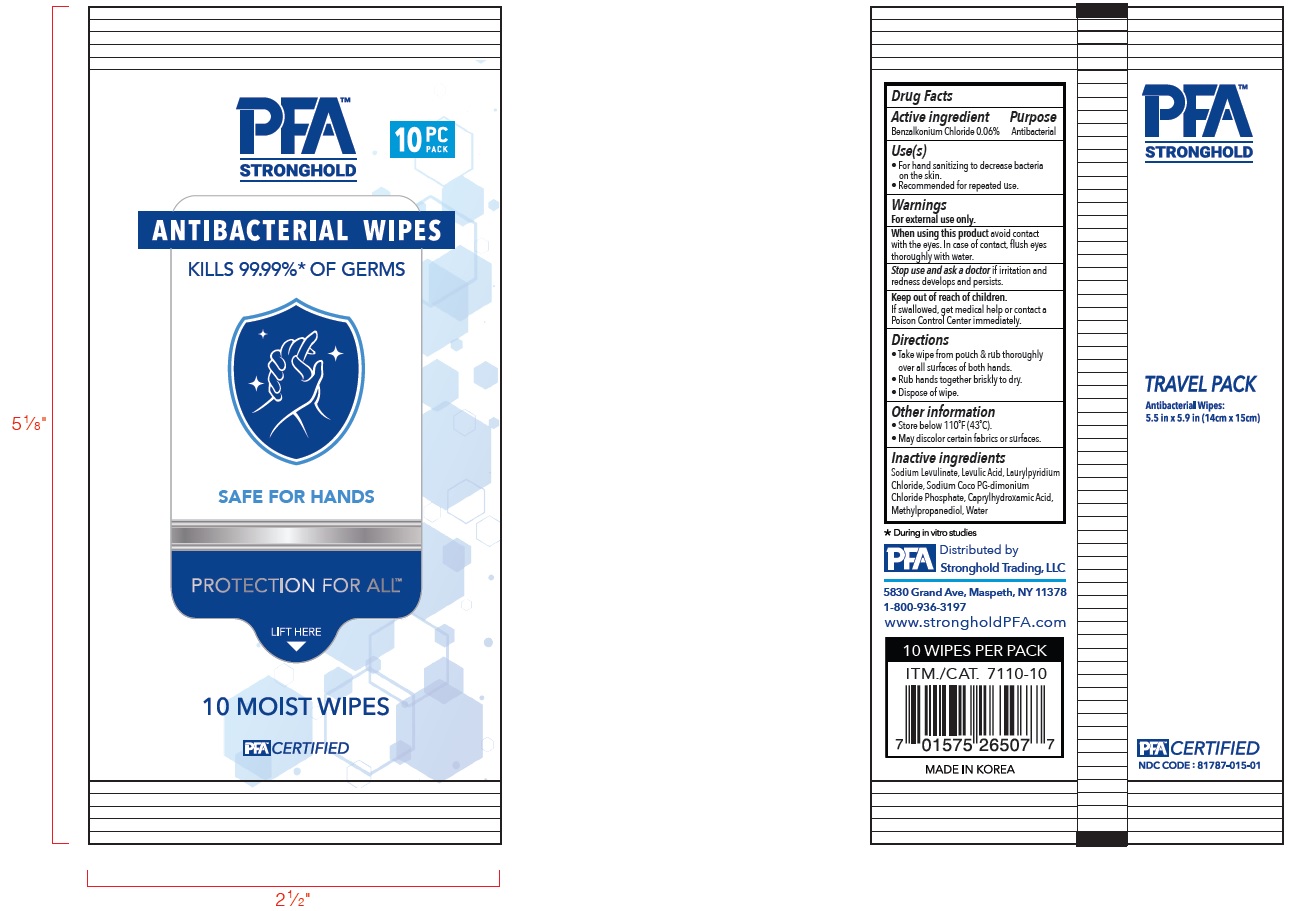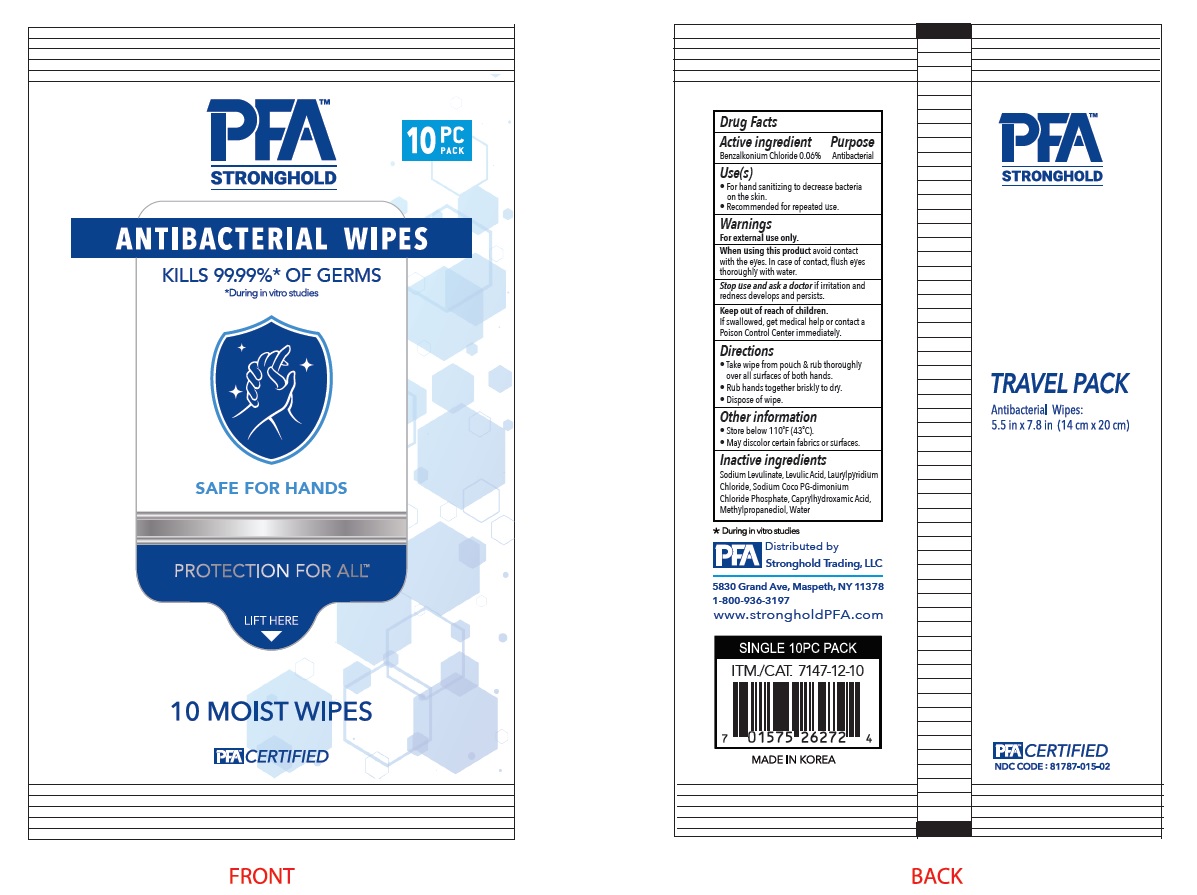 DRUG LABEL: PFA ANTIBACTERIAL WIPES
NDC: 81787-015 | Form: CLOTH
Manufacturer: Korea Living Goods Lab
Category: otc | Type: HUMAN OTC DRUG LABEL
Date: 20211104

ACTIVE INGREDIENTS: Benzalkonium chloride 0.0006 1/1 1
INACTIVE INGREDIENTS: Water; Sodium Levulinate; Methylpropanediol; Caprylhydroxamic Acid

ACTIVE INGREDIENT

Benzalkonium chloride 0.06%

INACTIVE INGREDIENTS

Sodium Levulinate, Levulic Acid, Laurylpyridium Chloride, Sodium Coco PG-dimonium Chloride Phosphate, Caprylhydroxamic Acid, Methylpropanediol, Water

PURPOSE

Antibacterial

WARNINGS

For external use only.
--------------------------------------------------------------------------------------------------------
When using this product avoid contact with the eyes. In case of contact, flush eyes thoroughly with water
--------------------------------------------------------------------------------------------------------
Stop use and ask a doctor if irritation and redness develops and persists.

KEEP OUT OF REACH OF CHILDREN

If swallowed, get medical help or contact a Poison Control Center immediately.

Use(s)

■ For hand sanitizing to decrease bacteria on the skin.
■ Recommeded for repeated use.

Directions

■ Take wipe from pouch & rub thoroughly over all surfaces of both hands.
■ Rub hands together briskly to dry.
■ Dispose of wipe

Other information

■ Store below 110℉(43℃)
■ May discolor certain fabrics or surfaces.